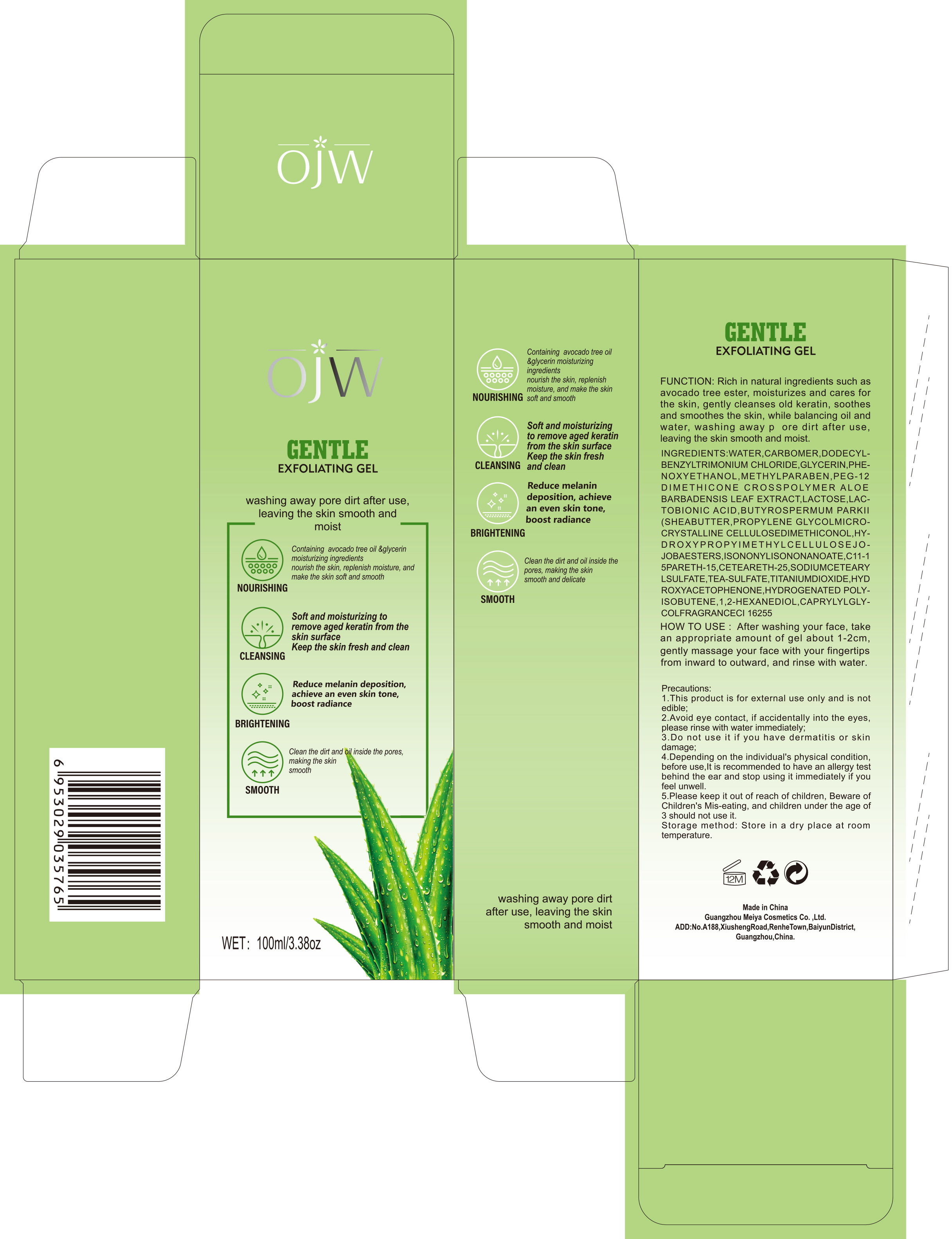 DRUG LABEL: Antiperspirant
NDC: 84673-009 | Form: EMULSION
Manufacturer: Guangzhou Meiya Cosmetics Co. ,Ltd.
Category: otc | Type: HUMAN OTC DRUG LABEL
Date: 20240925

ACTIVE INGREDIENTS: ALUMINUM CHLOROHYDRATE 60 mg/1 mL
INACTIVE INGREDIENTS: WATER 75.15 mg/1 mL; GLYCERIN 3 mg/1 mL; ALLANTOIN 0.2 mg/1 mL; ALCOHOL 5 mg/1 mL; PEG/PPG-14/7 DIMETHYL ETHER 1 mg/1 mL; ETHYLHEXYLGLYCERIN 0.05 mg/1 mL; TREHALOSE 2 mg/1 mL; PHENOXYETHANOL 0.45 mg/1 mL; METHYLPARABEN 0.15 mg/1 mL

ACTIVE INGREDIENT

ALUMINUM CHLOROHYDRATE 4.4%

PURPOSE

Function:Immerse yourself in a fragrant garden. the texture light and softness,fresh enough.Sprayed to drive away the smell, releases the faint fragrance slowly, keep people away from body odor and embarrassment,bring you an elegant life with no fear.

INDICATIONS AND USAGE

HOW TO USE : Shake gently before use, 15cm away from the skin, spray under the armpits or sweaty body skin, avoid touching the eyes and face; can be used after travel or shower.

WARNINGS

1. This product is for external use only and is not edible;

2. Avoid eye contact, if accidentally into the eyes, please rinse with water immediately;

3. Do not use it if you have dermatitis or skin damage;

4. Depending on the individual's physical condition, before use,It is recommended to have an allergy test behind the ear and stop using it immediately if you feel unwell.

5. Please keep it out of reach of children, Beware of Children's Mis-eating, and children under the age of 3 should not use it.

6.Please note: Do not spray into the mouth, eyes, nose.High pressure content, explosive at temperatures above 50℃ do not puncture, do not be heated.

STOP USE

1. Avoid eye contact, if accidentally into the eyes, please rinse with water immediately;

2. Do not use it if you have dermatitis or skin damage;

3. Depending on the individual's physical condition, before use,It is recommended to have an allergy test behind the ear and stop using it immediately if you feel unwell.

DO NOT USE

1. Avoid eye contact, if accidentally into the eyes, please rinse with water immediately;

2. Do not use it if you have dermatitis or skin damage;

3. Depending on the individual's physical condition, before use,It is recommended to have an allergy test behind the ear and stop using it immediately if you feel unwell.

4. Please keep it out of reach of children, Beware of Children's Mis-eating, and children under the age of 3 should not use it.

WHEN USING

Please note: Do not spray into the mouth, eyes, nose.High pressure content, explosive at temperatures above 50℃ do not puncture, do not be heated.

KEEP OUT OF REACH OF CHILDREN

Please keep it out of reach of children, Beware of Children's Mis-eating, and children under the age of 3 should not use it.